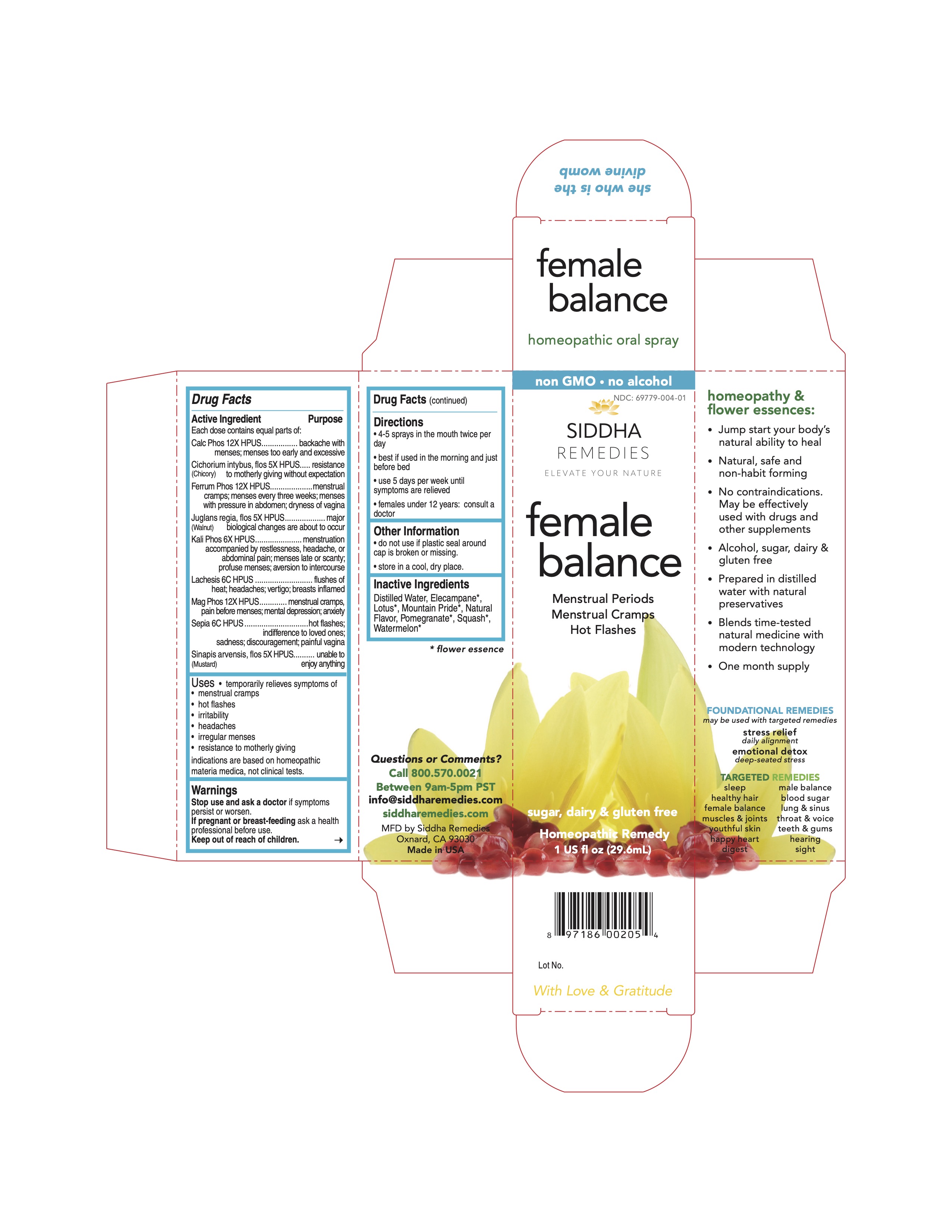 DRUG LABEL: female balance
NDC: 69779-004 | Form: SPRAY
Manufacturer: Siddha Flower Essences LLC
Category: homeopathic | Type: HUMAN OTC DRUG LABEL
Date: 20251231

ACTIVE INGREDIENTS: TRIBASIC CALCIUM PHOSPHATE 12 [hp_X]/29.6 mL; CICHORIUM INTYBUS FLOWER 5 [hp_X]/29.6 mL; FERROSOFERRIC PHOSPHATE 12 [hp_X]/29.6 mL; JUGLANS REGIA FLOWERING TOP 5 [hp_X]/29.6 mL; POTASSIUM PHOSPHATE, DIBASIC 6 [hp_X]/29.6 mL; LACHESIS MUTA VENOM 6 [hp_C]/29.6 mL; MAGNESIUM PHOSPHATE, DIBASIC TRIHYDRATE 12 [hp_X]/29.6 mL; SEPIA OFFICINALIS JUICE 6 [hp_C]/29.6 mL; SINAPIS ARVENSIS FLOWERING/FRUITING TOP 5 [hp_X]/29.6 mL
INACTIVE INGREDIENTS: NELUMBO NUCIFERA FLOWER; PUNICA GRANATUM FLOWER; WATER; WATERMELON

Drug Facts

Active Ingredient

Each does contains equal parts of:
Calc Phos 12X HPUS
Cichorium intybus, flos (Chicory) 5X HPUS
Ferrum Phos, 12X HPUS
Juglans regia, flos (Walnut) 5X HPUS
Kali Phos 6X HPUS
Lachesis 6C HPUS
Mag Phos 12X HPUS
Sepia 6C HPUS
Sinapis arvensis, flos (Mustard) 5X HPUS

PURPOSE

Each does contains equal parts of:
Calc Phos 12X HPUS...........................................backache with menses; menses too early and excessive
Cichorium intybus, flos (Chicory) 5X HPUS............resistance to motherly giving without expectation
Ferrum Phos, 12X HPUS......................................menstrual cramps; menses every three weeks; menses with pressure in abdomen; dryness of vagina
Juglans regia, flos (Walnut) 5X HPUS....................major biological changes are about to occur
Kali Phos 6X HPUS.............................................menstruation accompanied by restlessness, headache, or abdominal pain; menses late or scanty; profuse menses; aversion to intercourse
Lachesis 6C HPUS...............................................flushes of heat; headaches; vertigo; breasts inflamed
Mag Phos 12X HPUS...........................................menstrual cramps; pain before menses; mental depression; anxiety
Sepia 6C HPUS...................................................hot flashes; indifference to loved ones; sadness; discouragement; painful vagina
Sinapis arvensis, flos (Mustard) 5X HPUS..............unable to enjoy anything

Uses

- temporarily relieves symptoms of
- menstrual cramps
- hot flashes
- irritability
- headaches
- irregular menses
- resistance to motherly giving

indications are based on homeopathic materia medica, not clinical tests.

Warnings

Stop use and ask a doctor if symptoms persist or worsen.

PREGNANCY OR BREAST FEEDING

If pregnant or breast-feeding ask a health professional before use.

Keep out of reach of children.

Directions

- 4-5 sprays in the mouth twice per day
- best if used in the morning and just before bed
- use 5 days per week until symptoms are relieved
- females under 12 years: consult a doctor

Other Information

- do not use if plastic seal around cap is broken or missing.
- store in a cool, dry place.

Inactive Ingredients

Elecampane*, Lotus*, Mountain Pride*, Natural Flavor, Pomegranate*, Purified Water, Squash*, Watermelon*

*flower essence

Questions or Comments?

Call 800.570.0021
Between 9am-5pm PST
info@siddhaflowers.com
siddhaflowers.com
MFD by Siddha Flower Essences
Oxnard, CA 93030
Made in USA

Side Panel

homeopathy and flower essences:

- Jump start your body's natural ability to heal
- Natural, safe, and non-habit forming
- No contraindications. May be effectively used with drugs and other supplement
- Alcohol, sugar, dairy and gluten-free
- Prepared in purified water with natural preservatives
- Blends time-tested natural medicine with modern technology
- One month supply

FOUNDATIONAL REMEDIES

may be used with targeted relief

stress relief
daily alignment
emotional detox
deep-seated stress

TARGETED REMEDIES

sleep male balance
healthy hair blood sugar
female balance lung and sinus
muscles and joints throat and voice
youthful skin teeth and gums
happy heart hearing
digest sight

Principal Display Panel

non GMO - no alcohol
siddha cell salts + flower essences

female balance

Menstrual Periods
Menstrual Cramps
Hot Flashes
sugar, dairy and gluten free
Homeopathic Remedy
1 US fl oz (29.6mL)